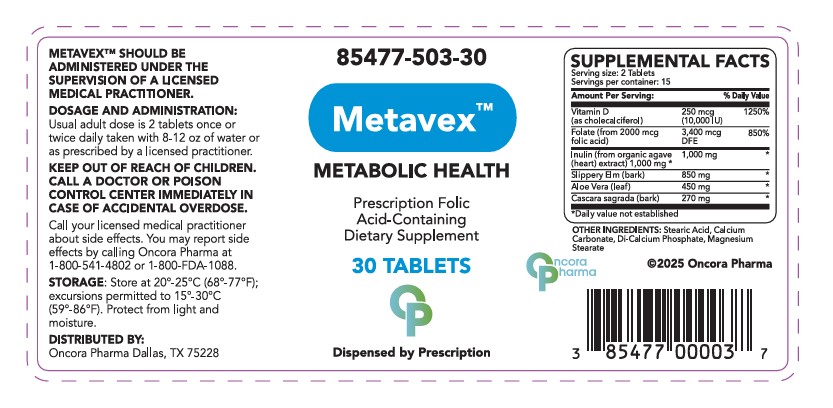 DRUG LABEL: METAVEX
NDC: 85477-503 | Form: TABLET
Manufacturer: Oncora Pharma, LLC
Category: prescription | Type: HUMAN PRESCRIPTION DRUG LABEL
Date: 20260106

ACTIVE INGREDIENTS: CHOLECALCIFEROL .125 mg/1 1; FOLIC ACID 1 mg/1 1; BLUE AGAVE INULIN (AGAVE TEQUILANA) 500 mg/1 1; ELM 425 mg/1 1; ALOE FEROX LEAF 225 mg/1 1; RHAMNUS CATHARTICA BARK 135 mg/1 1
INACTIVE INGREDIENTS: STEARIC ACID; CALCIUM CARBONATE; CALCIUM PHOSPHATE; MAGNESIUM STEARATE

Metavex

DESCRIPTION

Metavex™ is a prescription folic acid–containing dietary supplement intended to support metabolic health. Each tablet contains a combination of vitamins, minerals, and botanical ingredients formulated to provide nutritional support.

INDICATIONS AND USAGE

Metavex™ is indicated as a prescription dietary supplement for the dietary management of individuals with metabolic health needs where folic acid supplementation is appropriate.

Administration:
Take two (2) tablets daily with a 12-ounce glass of water, or as directed by a licensed healthcare practitioner.

CONTRAINDICATIONS

Metavex™ is contraindicated in patients with known hypersensitivity to any of its components.

WARNINGS

Metavex™ should be administered under the supervision of a licensed medical practitioner.

Patients should not exceed the recommended dosage.

If adverse reactions occur, discontinue use and consult a healthcare professional.

Precautions

Folic Acid and Vitamin B12 Deficiency:
Folic acid administered alone may be inappropriate for the treatment of pernicious anemia or other megaloblastic anemias where vitamin B12 deficiency is present. Doses of folic acid greater than 0.1 mg daily may mask hematologic signs of pernicious anemia while neurological manifestations continue to progress.

Patients with underlying medical conditions or those taking other medications should consult their healthcare provider prior to use.

DOSAGE AND ADMINISTRATION

Take two (2) tablets daily with a 12-ounce glass of water, or as directed by a licensed healthcare practitioner.

HOW SUPPLIED

Metavex™ is supplied as tan, oval tablets in bottles of 30 tablets.

NDC 85477-503-30

Display Panel

Metavex™

METABOLIC HEALTH

Prescription Folic Acid-Containing
Dietary Supplement

30 Tablets

Dispensed by Prescription

Distributed by:
Oncora Pharma
Dallas, TX 75228

NDC 85477-503-30